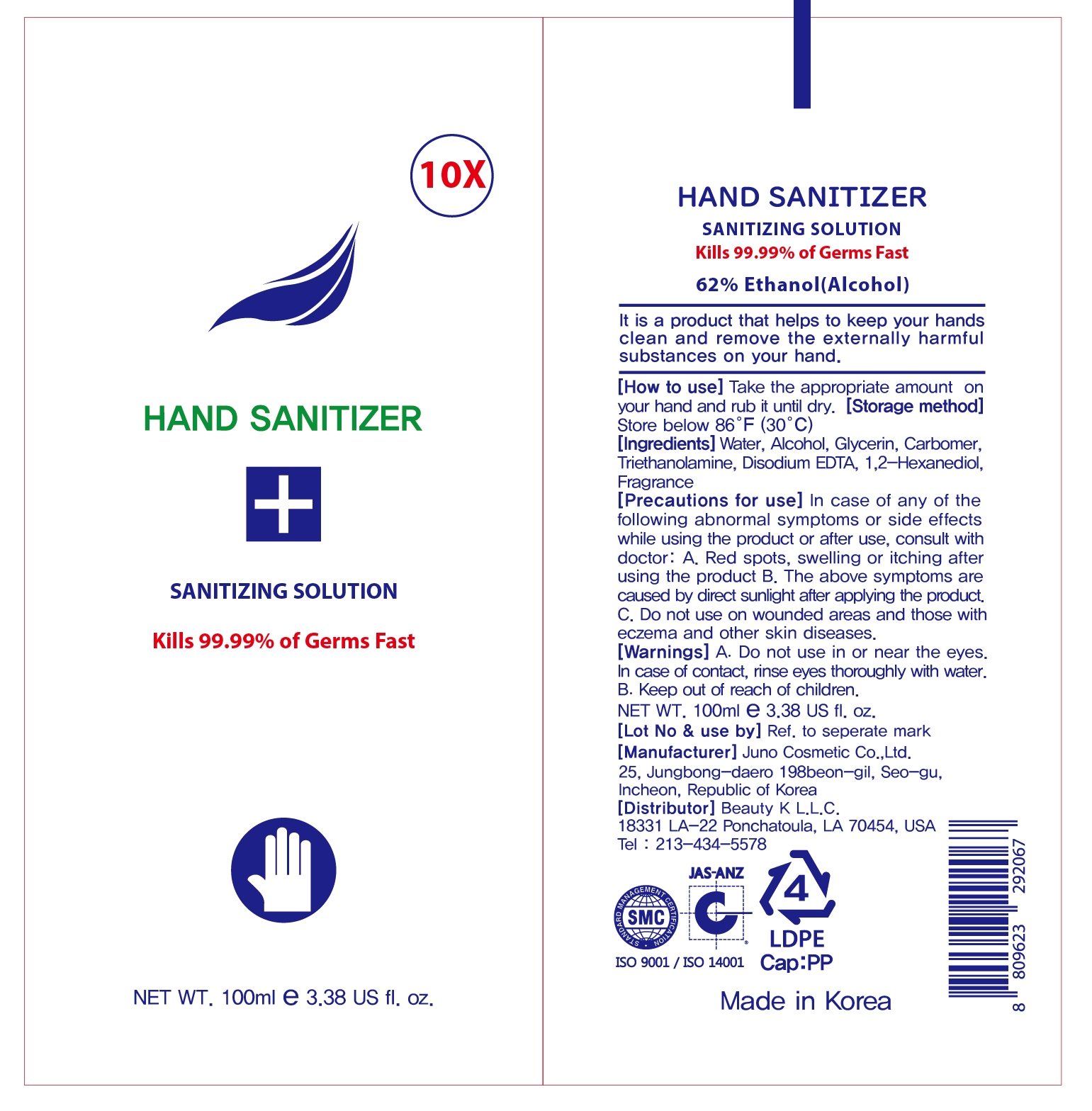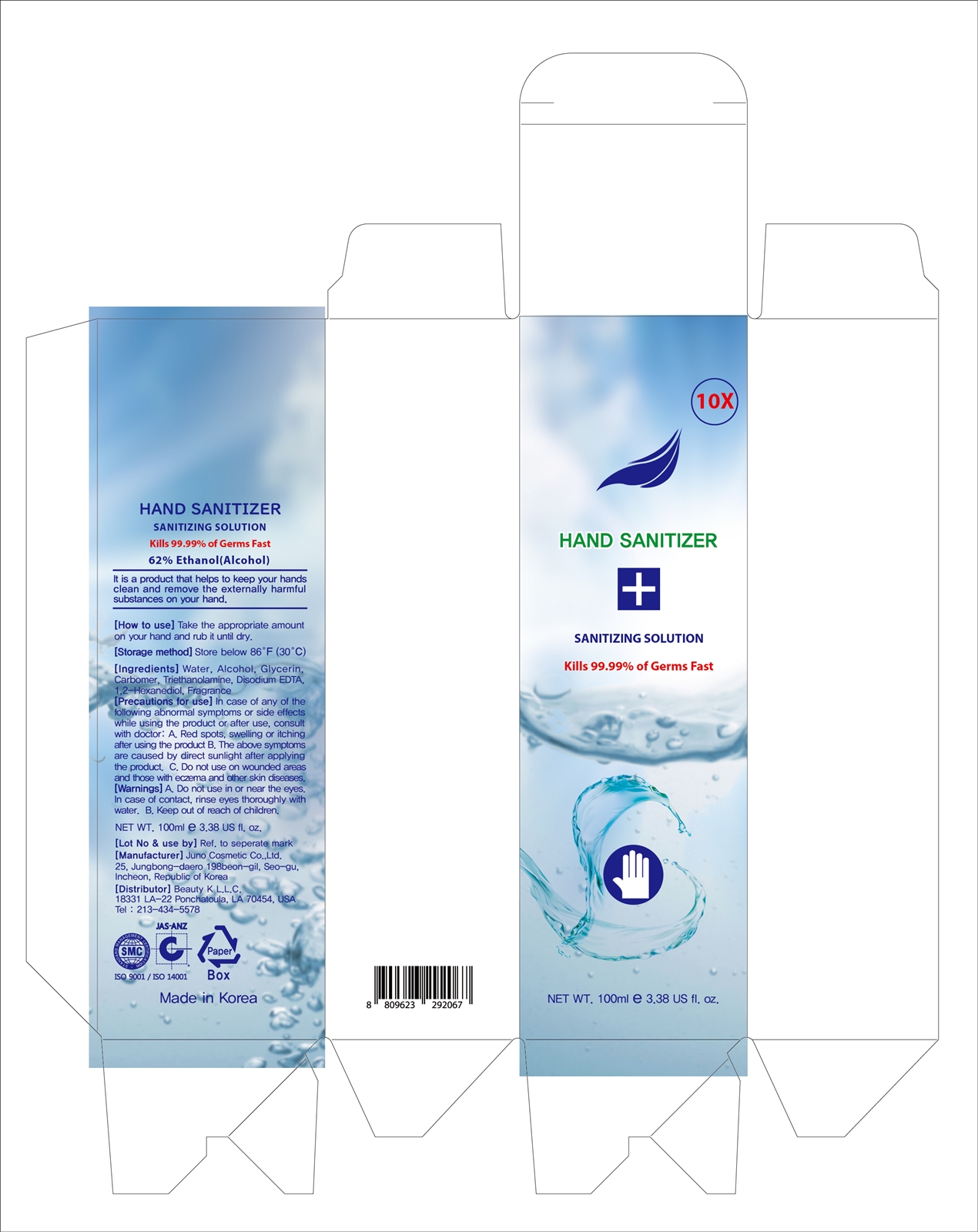 DRUG LABEL: Hand Cleaner
NDC: 77821-201 | Form: GEL
Manufacturer: JUNO COSMETICS
Category: otc | Type: HUMAN OTC DRUG LABEL
Date: 20200514

ACTIVE INGREDIENTS: ALCOHOL 62 mL/100 mL
INACTIVE INGREDIENTS: EDETATE DISODIUM ANHYDROUS; TROLAMINE; FRAGRANCE LAVENDER & CHIA F-153480; CARBOMER HOMOPOLYMER, UNSPECIFIED TYPE; GLYCERIN; WATER; 1,2-HEXANEDIOL

Active Ingredient

Alcohol 62%

Purpose

Antiseptic

Use

It is a product that helps to keep your hands clean and remove the externally harmful substances on your hand.

How to use

Take the appropriate amount on your hand and rub it until dry.

Storage method

Store below 86F (30C)

Precautions for use

In case of any of the following abnormal symptoms or side effects while using the product or after use, consult with doctor:

A. Red spots, swelling or itching after using the product.

Precautions for use

B. The above symptoms are caused by direct sunlight after applying the product.

Precautions for use

C. Do not use on wounded areas and those with eczema and other skin diseases.

Warnings

A. Do not use in or near the eyes. In case of contact, rinse eyes thoroughly with water.

Warnings

B. Keep out of reach of children.

Ingredients

Water, Glycerin, Carbomer, Triethanolamine, Disodium EDTA, 1,2-Hexanediol, Fragrance